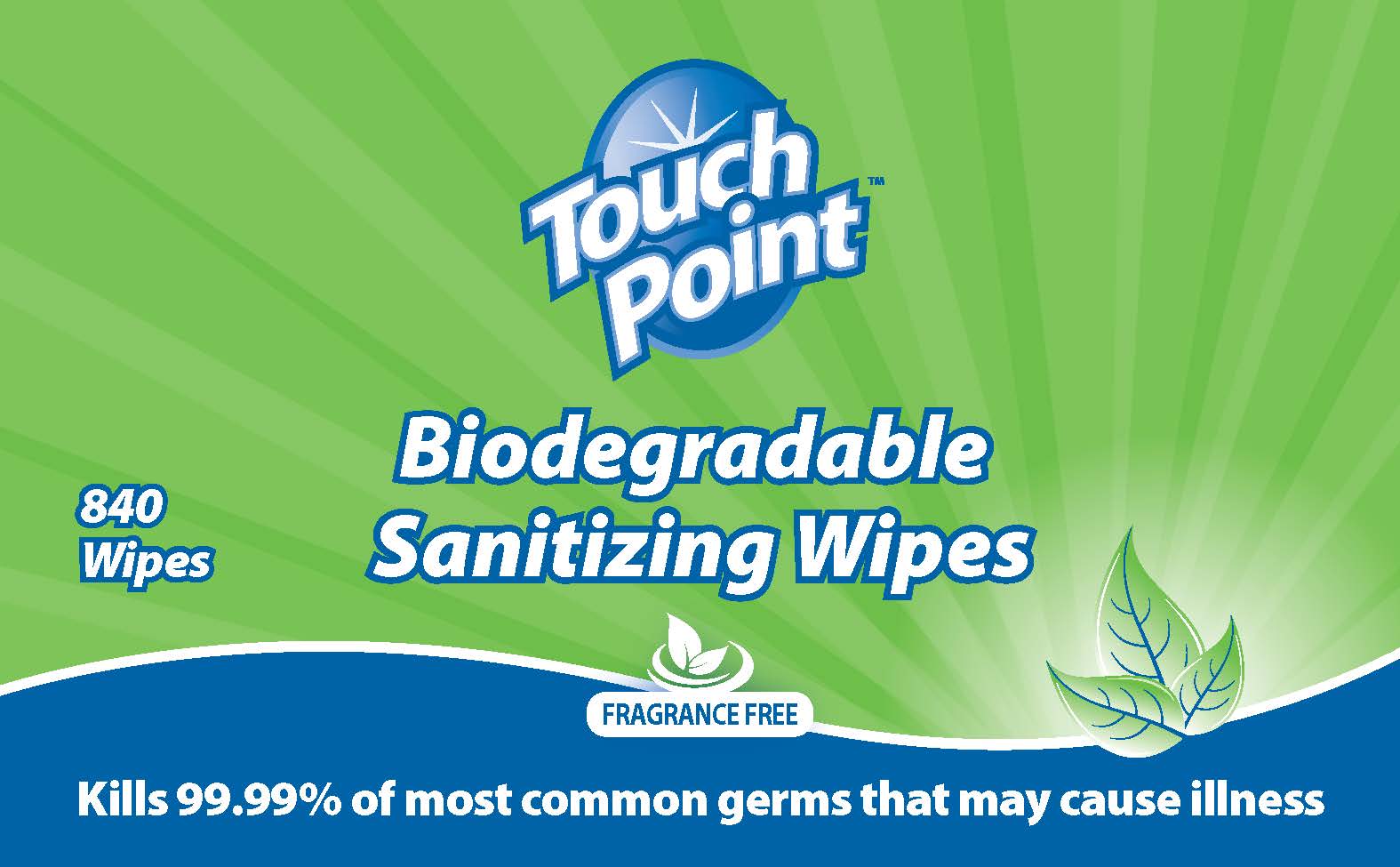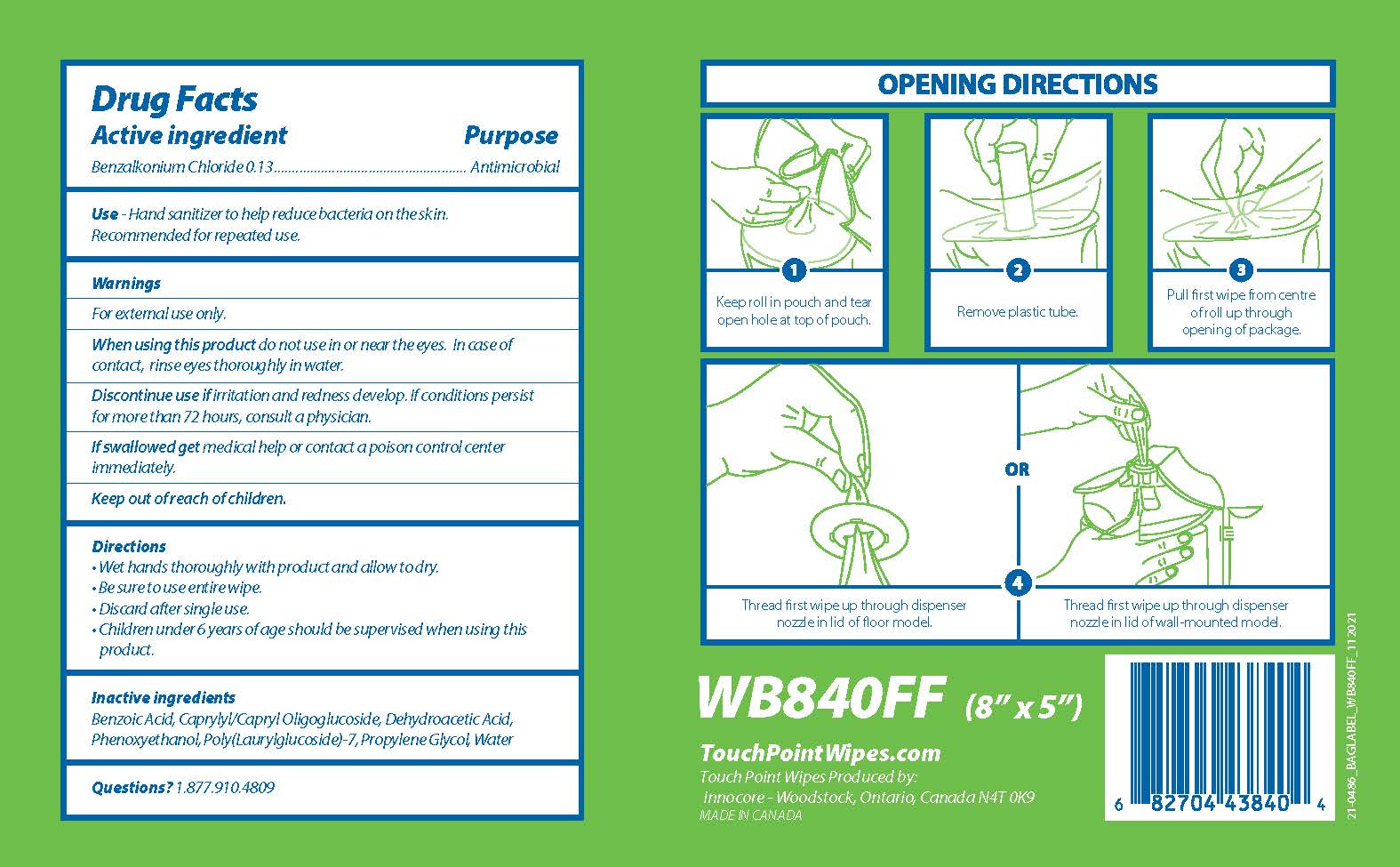 DRUG LABEL: Touchpoint Biodegradable Sanitizing Wipes
NDC: 70924-004 | Form: CLOTH
Manufacturer: Innocore Sales & Marketing Inc
Category: otc | Type: HUMAN OTC DRUG LABEL
Date: 20250619

ACTIVE INGREDIENTS: BENZALKONIUM CHLORIDE 1.3 mg/1 1
INACTIVE INGREDIENTS: WATER; PROPYLENE GLYCOL; CAPRYLYL/CAPRYL OLIGOGLUCOSIDE; POLY(LAURYLGLUCOSIDE)-7; PHENOXYETHANOL; BENZOIC ACID; DEHYDROACETIC ACID

Touchpoint Biodegradable Sanitizing Wipes

Drug Facts

Active ingredient

Benzalkonium Chloride 0.13 %

Purpose

Antimicrobal

Use

Hand sanitizer to help reduce bacteria on the skin.

Recommended for repeated use.

Warnings

For external use only.

When using this product do not use in or near the eyes. In case of contact, rinse eyes thoroughly in water.

STOP USE

Discontinue use if irritation and redness develop. If conditions persist for more than 72 hours, consult a physician.

If swallowed get medical help or contact a poison control center immediately.

Keep out of reach of children.

Directions

- Wet hands thoroughly with product and allow to dry.
- Be sure to use entire wipe.
- Discard after single use.
- Children under 6 years of age should be supervised when using this product.

Inactive ingredients

Benzoic Acid, Caprylyl/Capryl Oligoglucoside, Dehydroacetic Acid, Phenoxyethanol, Poly(Laurylglucoside)-7, Propylene Glycol, Water

Questions?

1.877.910.4809

PACKAGE LABEL

Touch
Point TM

Biodegradable

Sanitizing Wipes

840 Wipes

Fragrance Free

Kills 99.99% of most common germs that may cause illness

OPENING DIRECTIONS

1

Keep roll in pouch and tear

open hole at top of pouch

2

Remove plastic tube.

3

Pull first wipe from centre

of roll up through

opening of package

OR

4

Thread first wipe up through dispenser

nozzle in lid of floor model.

Thread first wipe up through dispenser

nozzle in lid of wall-mounted model.

WB840FF (8" x 5")

TouchPointWipes.com
Touch Point Wipes Produced by:
Innocore - Woodstock, Ontario, Canada N4T 0K9
MADE IN CANADA